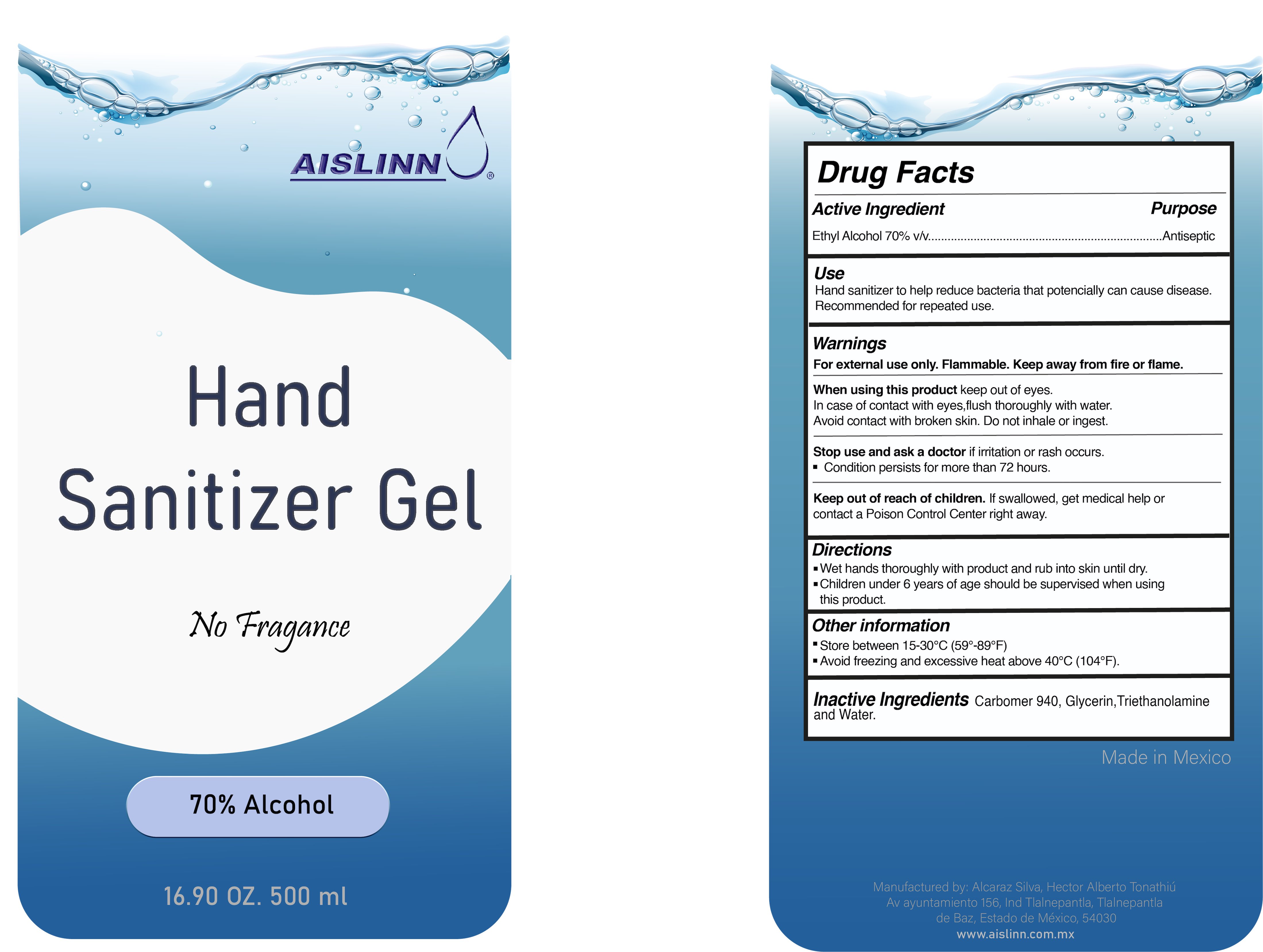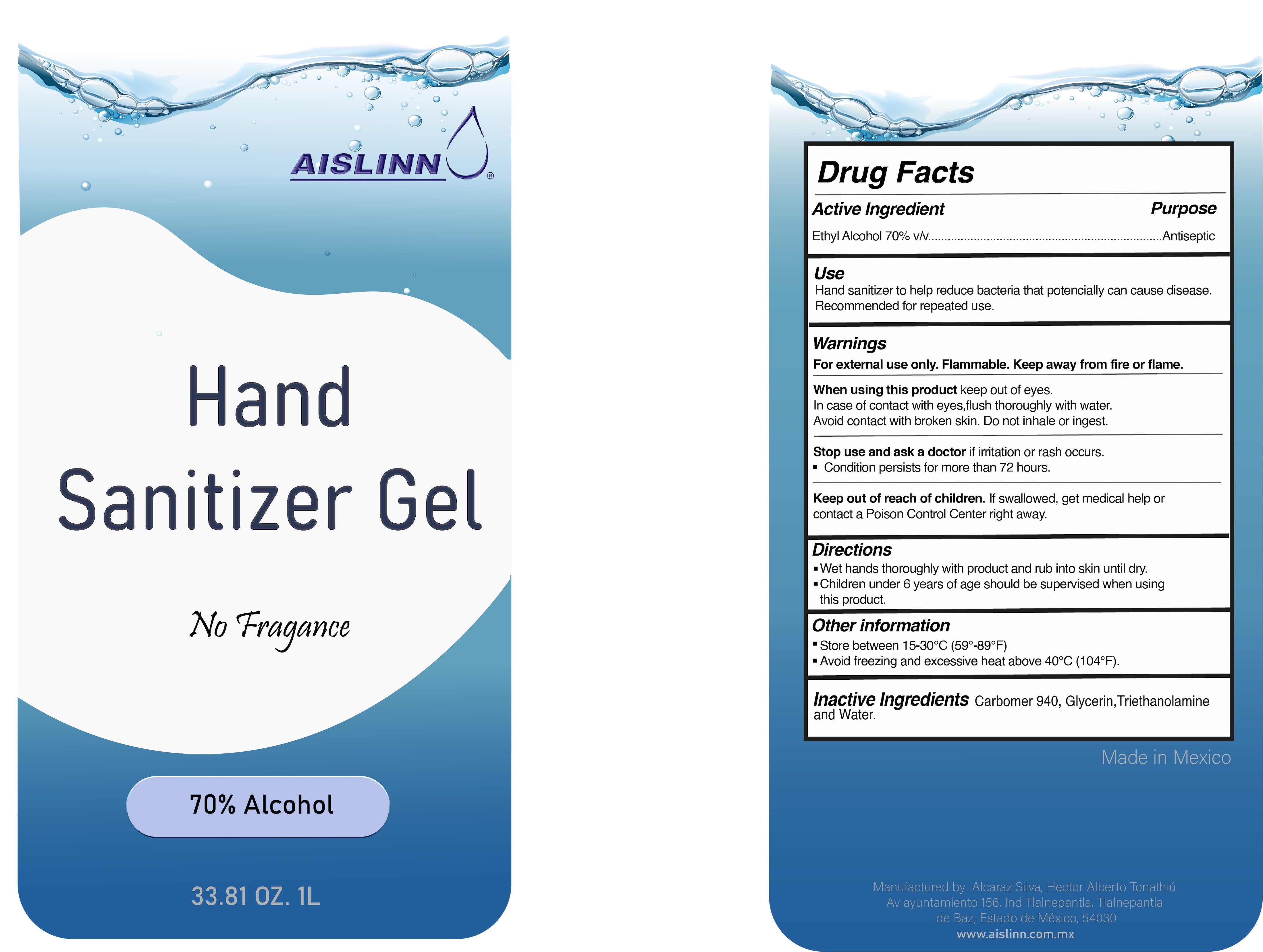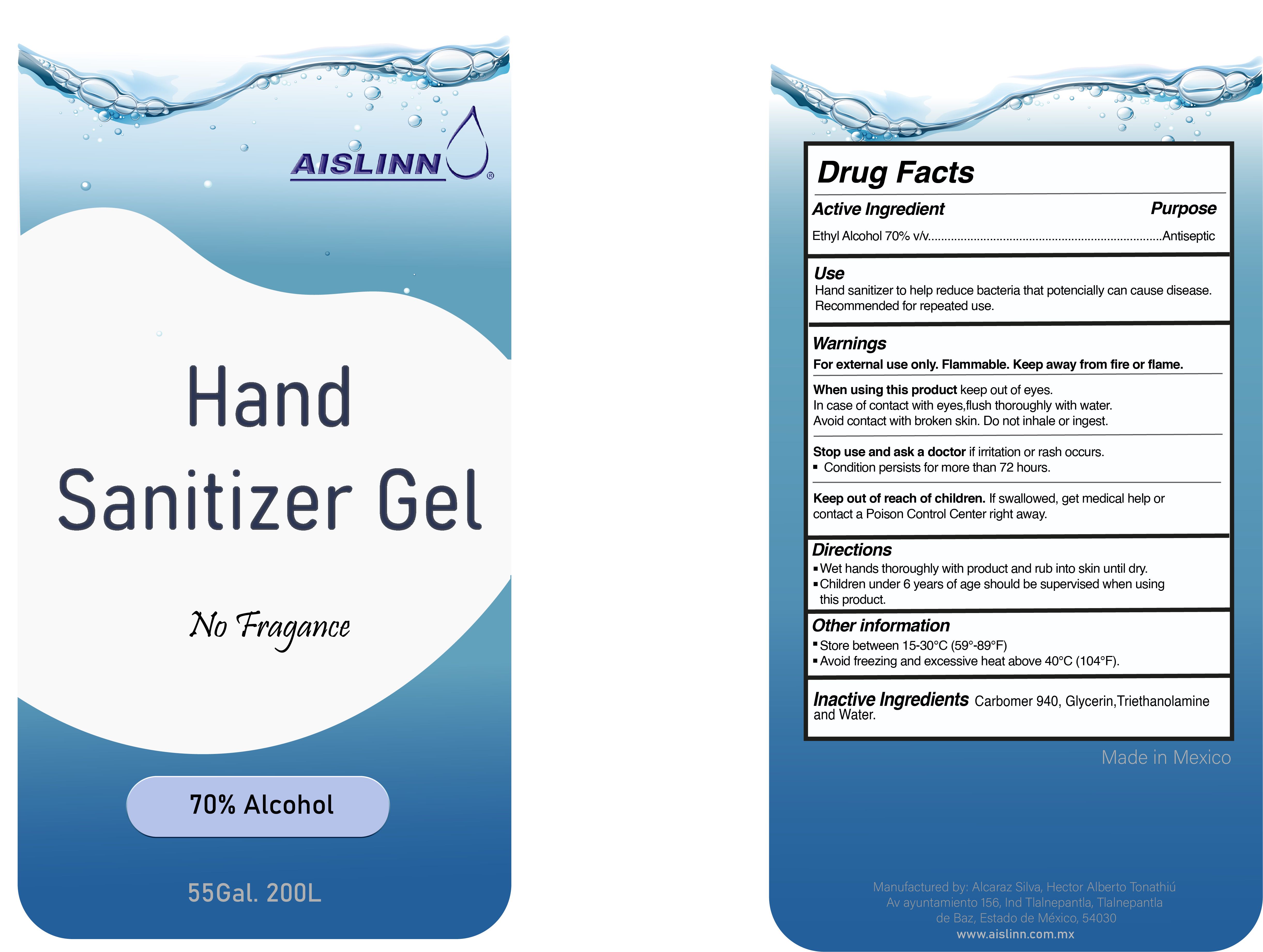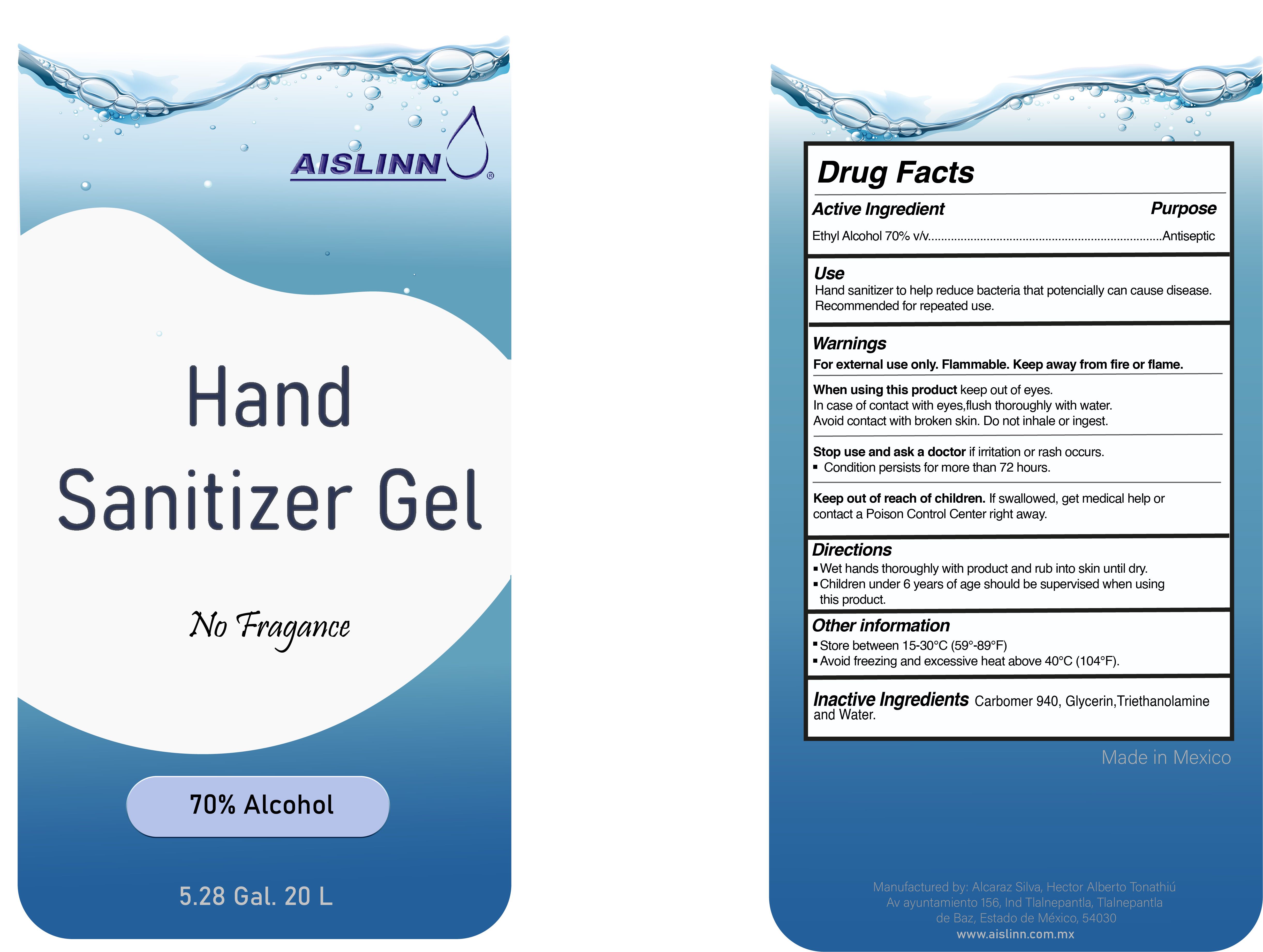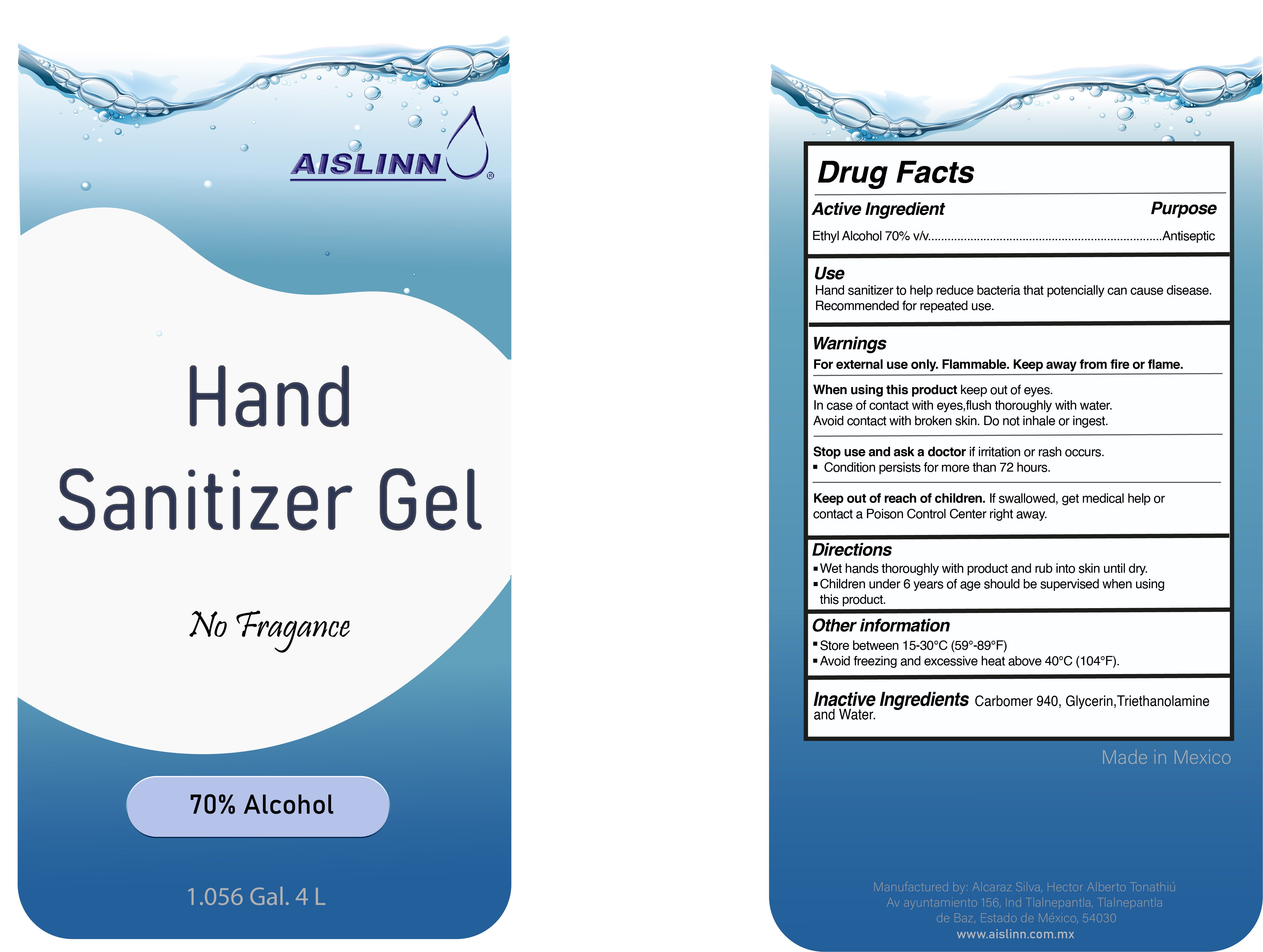 DRUG LABEL: Aislinn Hand Sanitizer Gel
NDC: 79664-100 | Form: GEL
Manufacturer: Alcaraz Silva, Hector Alberto Tonathiú
Category: otc | Type: HUMAN OTC DRUG LABEL
Date: 20200728

ACTIVE INGREDIENTS: ALCOHOL 70 mL/100 mL
INACTIVE INGREDIENTS: WATER; TROLAMINE; CARBOMER 940; GLYCERIN

Aislinn Hand Sanitizer Gel - 70% Alcohol

ACTIVE INGREDIENT

Ethyl alcohol 70% v/v

PURPOSE

Antiseptic

INDICATIONS AND USAGE

Hand Sanitizer to help reduce bacteria that potentially can cause disease
Recommended for repeated use

WARNINGS

For external use only.

Flammable. Keep away from fire or flame.

When using this product keep out of eyes.

In case of contact with eyes, flush thoroughly with water

Avoid contact on broken skin. Do not inhale or ingest.

Stop use and ask a doctor if irritation or rash occurs.

Condition persists for more than 72 hours.

Keep out of reach of children. If swallowed, get medical help or contact a Poison Control Center right away.

Directions

Wet hand thoroughly with product and rub into skin until dry.

Children under 6 years of age should be supervised when using this product.

OTHER SAFETY INFORMATION

Store between 15-30ºC (59-89ºF)

Avoid freezing and excessive heating 40ºC (104ºF)

INACTIVE INGREDIENT

Carbomer 940, Glycerin, Triethanolamine and Water

PACKAGE LABEL

NDC 79664-100-01 500mL

NDC 79664-100-02 1000mL

NDC 79664-100-03 4000mL

NDC 79664-100-04 20000mL

NDC 79664-100-05 200000mL